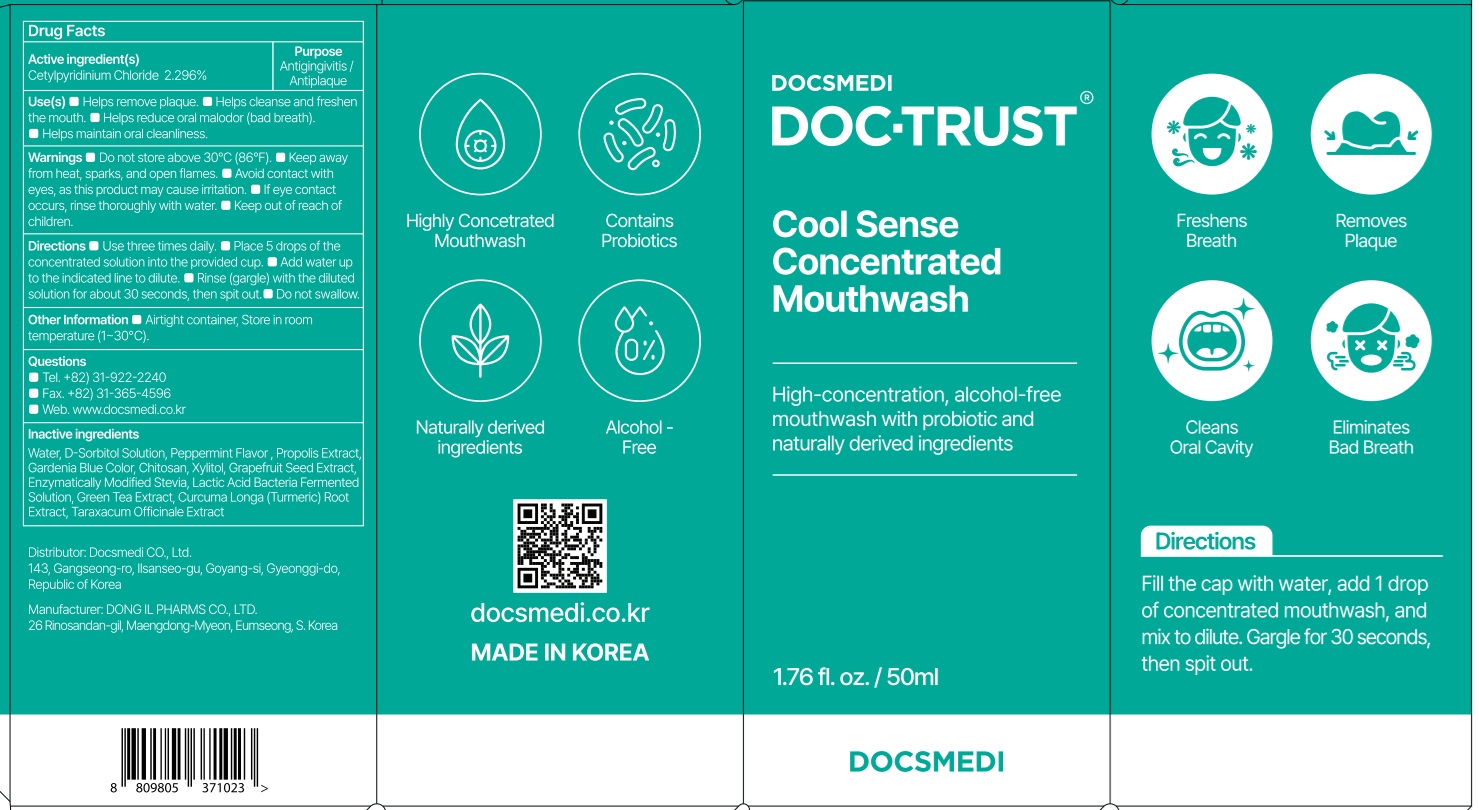 DRUG LABEL: Cool Sense Concentrated
NDC: 73242-1125 | Form: MOUTHWASH
Manufacturer: DONG IL PHARMS CO.,LTD
Category: otc | Type: HUMAN OTC DRUG LABEL
Date: 20251208

ACTIVE INGREDIENTS: CETYLPYRIDINIUM CHLORIDE 2.296 g/100 mL
INACTIVE INGREDIENTS: WATER; SORBITOL

Active ingredient(s)

Cetylpyridinium Chloride 2.296%

Inactive ingredients

Water, D-Sorbitol Solution, Peppermint Flavor , Propolis Extract, Gardenia Blue Color, Chitosan, Xylitol, Grapefruit Seed Extract, Enzymatically Modified Stevia, Lactic Acid Bacteria Fermented Solution, Green Tea Extract, Curcuma Longa (Turmeric) Root Extract, Taraxacum Officinale Extract

Purpose

Antigingivitis / Antiplaque

Warnings

■ Do not store above 30°C (86°F).

■ Keep away from heat, sparks, and open flames.

■ Avoid contact with eyes, as this product may cause irritation.

■ If eye contact occurs, rinse thoroughly with water.

■ Keep out of reach of children.

Keep out of reach of children.

INDICATIONS AND USAGE

Use(s)

■ Helps remove plaque

■ Helps cleanse and freshen the mouth

■ Helps reduce oral malodor (bad breath)

■ Helps maintain oral cleanliness

Directions

■ Use three times daily.

■ Place 5 drops of the concentrated solution into the provided cup.

■ Add water up to the indicated line to dilute.

■ Rinse (gargle) with the diluted solution for about 30 seconds, then spit out.

■ Do not swallow.

Other Information

■ Airtight container, Store in room temperature (1~30℃)

Questions

■ Tel: +82) 31-922-2240, Fax: 82-031-365-4596

■ Fax: +82) 31-365-4596

■ Web: docsmedi.co.kr